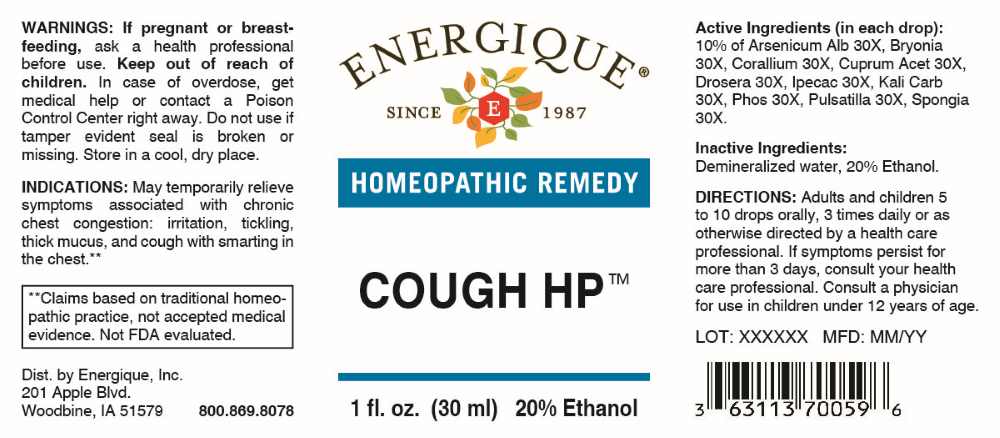 DRUG LABEL: Cough
NDC: 44911-0319 | Form: LIQUID
Manufacturer: Energique, Inc.
Category: homeopathic | Type: HUMAN OTC DRUG LABEL
Date: 20251124

ACTIVE INGREDIENTS: ARSENIC TRIOXIDE 30 [hp_X]/1 mL; BRYONIA ALBA ROOT 30 [hp_X]/1 mL; CORALLIUM RUBRUM EXOSKELETON 30 [hp_X]/1 mL; CUPRIC ACETATE 30 [hp_X]/1 mL; DROSERA ROTUNDIFOLIA WHOLE 30 [hp_X]/1 mL; IPECAC 30 [hp_X]/1 mL; POTASSIUM CARBONATE 30 [hp_X]/1 mL; PHOSPHORUS 30 [hp_X]/1 mL; PULSATILLA PRATENSIS WHOLE 30 [hp_X]/1 mL; SPONGIA OFFICINALIS SKELETON, ROASTED 30 [hp_X]/1 mL
INACTIVE INGREDIENTS: WATER; ALCOHOL

DRUG FACTS:

ACTIVE INGREDIENTS:

(in each drop): 10% of Arsenicum Album 30X, Bryonia (Alba) 30X, Corallium Rubrum 30X, Cuprum Aceticum 30X, Drosera (Rotundifolia) 30X, Ipecacuanha 30X, Kali Carbonicum 30X, Phosphorus 30X, Pulsatilla 30X, Spongia Tosta 30X.

PURPOSE:

May temporarily relieve symptoms associated with chronic chest congestion, irritation, tickling, thick mucus, and cough with smarting in the chest.**

**Claims based on traditional homeopathic practice, not accepted medical evidence. Not FDA evaluated.

WARNINGS:

If pregnant or breastfeeding, ask a health professional before use.

Keep out of reach of children. In case of overdose, get medical help or contact a Poison Control Center right away.

Do not use if tamper evident seal is broken or missing.

Store in a cool, dry place.

KEEP OUT OF REACH OF CHILDREN:

In case of overdose, get medical help or contact a Poison Control Center right away.

DIRECTIONS:

Adults and children 5 to 10 drops orally, 3 times daily or as otherwise directed by a health care professional. If symptoms persist for more than 3 days, consult your health care professional. Consult a physician for use in children under 12 years of age.

INDICATIONS:

May temporarily relieve symptoms associated with chronic chest congestion, irritation, tickling, thick mucus, and cough with smarting in the chest.**

**Claims based on traditional homeopathic practice, not accepted medical evidence. Not FDA evaluated.

INACTIVE INGREDIENTS:

Demineralized water, 20% Ethanol.

QUESTIONS:

Dist. by Energique, Inc.

201 Apple Blvd.

Woodbine, IA 51579

800.869.8078

PACKAGE LABEL DISPLAY:

ENERGIQUE
SINCE 1987
HOMEOPATHIC REMEDY
COUGH HP
1 fl. oz. (30 ml)